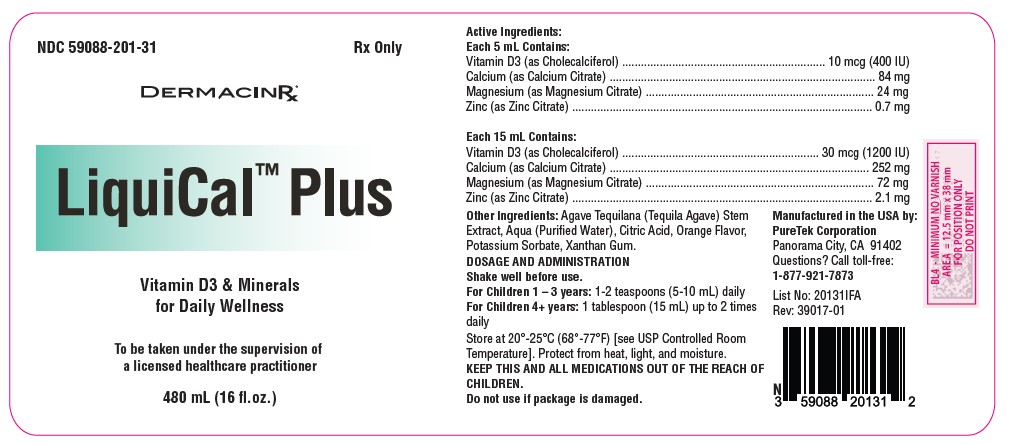 DRUG LABEL: LiquiCal Plus
NDC: 59088-201 | Form: LIQUID
Manufacturer: PureTek Corporation
Category: prescription | Type: HUMAN PRESCRIPTION DRUG LABEL
Date: 20240909

ACTIVE INGREDIENTS: CHOLECALCIFEROL 1200 [iU]/1 mL; ZINC CITRATE 2.1 mg/1 mL; MAGNESIUM CITRATE 72 mg/1 mL; CALCIUM CITRATE 252 mg/1 mL
INACTIVE INGREDIENTS: POTASSIUM SORBATE; WATER; ANHYDROUS CITRIC ACID; XANTHAN GUM; AGAVE TEQUILANA STEM

LiquiCal Plus
Liquid Multivitamin

DRUG DESCRIPTION:

LiquiCal™ Plus
Rx Only
Full Prescribing Information

Active Ingredients:
Each 5 mL Contains:
Vitamin D3 (as Cholecalciferol) ................................................................. 10 mcg (400 IU)
Calcium (as Calcium Citrate) ..................................................................................... 84 mg
Magnesium (as Magnesium Citrate) ......................................................................... 24 mg
Zinc (as Zinc Citrate) ................................................................................................ 0.7 mg

Each 15 mL Contains:
Vitamin D3 (as Cholecalciferol) ............................................................... 30 mcg (1200 IU)
Calcium (as Calcium Citrate) ................................................................................... 252 mg
Magnesium (as Magnesium Citrate) ......................................................................... 72 mg
Zinc (as Zinc Citrate) ................................................................................................ 2.1 mg

Other Ingredients: Agave Tequilana (Tequila Agave) Stem Extract, Aqua (Purified Water), Citric Acid, Orange Flavor, Potassium Sorbate, Xanthan Gum.

INDICATIONS:

LiquiCal™ Plus is indicated for dietary management of patients with unique nutritional needs requiring increased Vitamin D3 and essential minerals, including Calcium, Magnesium, and Zinc in a convenient liquid form for easy administration.

CLINICAL PHARMACOLOGY

Vitamin D3 is essential for calcium absorption in the gut and maintaining adequate serum calcium and phosphate concentrations, supporting bone mineralization and immune function.

Calcium is crucial for the development and maintenance of healthy bones and teeth, as well as muscle function.

Magnesium is important for muscle and nerve function, blood glucose control, and bone health.

Zinc supports normal growth and development, immune function, and wound healing.

CONTRAINDICATIONS:

This product is contraindicated in patients with a known hypersensitivity to any of the ingredients. LiquiCal™ Plus is contraindicated in patients with hypercalcemia, malabsorption syndrome, abnormal sensitivity to the toxic effects of vitamin D, and hypervitaminosis D.

WARNINGS AND PRECAUTIONS:

Tell your doctor if you have: kidney problems, thyroid disease. This medication should be used as directed during pregnancy or while breastfeeding. Consult your doctor.

ADVERSE REACTIONS:

Adverse reactions are rare but may include gastrointestinal disturbances such as nausea or constipation. If adverse reactions occur, discontinue use and consult a healthcare professional.

You should call your doctor for medical advice about serious adverse events. To report adverse side effects or to obtain product information, contact PureTek Corporation, at 1-877-921-7873 or FDA at 1-800-FDA-1088 or www.fda.gov/medwatch.

DOSAGE AND ADMINISTRATION:

Shake well before use.
For Children 1-3 years: 1-2 teaspoons (5-10 mL) daily
For Children 4+ years: 1 tablespoon (15 mL) up to 2 times daily

LiquiCal™ Plus should be administered under the supervision of a licensed healthcare practitioner.

HOW SUPPLIED:

LiquiCal™ Plus is available in a 480 mL white HDPE bottle with NDC 59088-201-31.

STORAGE:

KEEP THIS AND ALL MEDICATIONS OUT OF THE REACH OF CHILDREN.
Store at 20°-25°C (68°-77°F) [see USP Controlled Room Temperature].
Protect from heat, light, and moisture.
Tamper Evident: Do not use if the seal is broken or missing

LiquiCal™ Plus

Manufactured in the USA by:
PureTek Corporation
Panorama City, CA 91402
For questions or information call toll-free: 877-921-7873